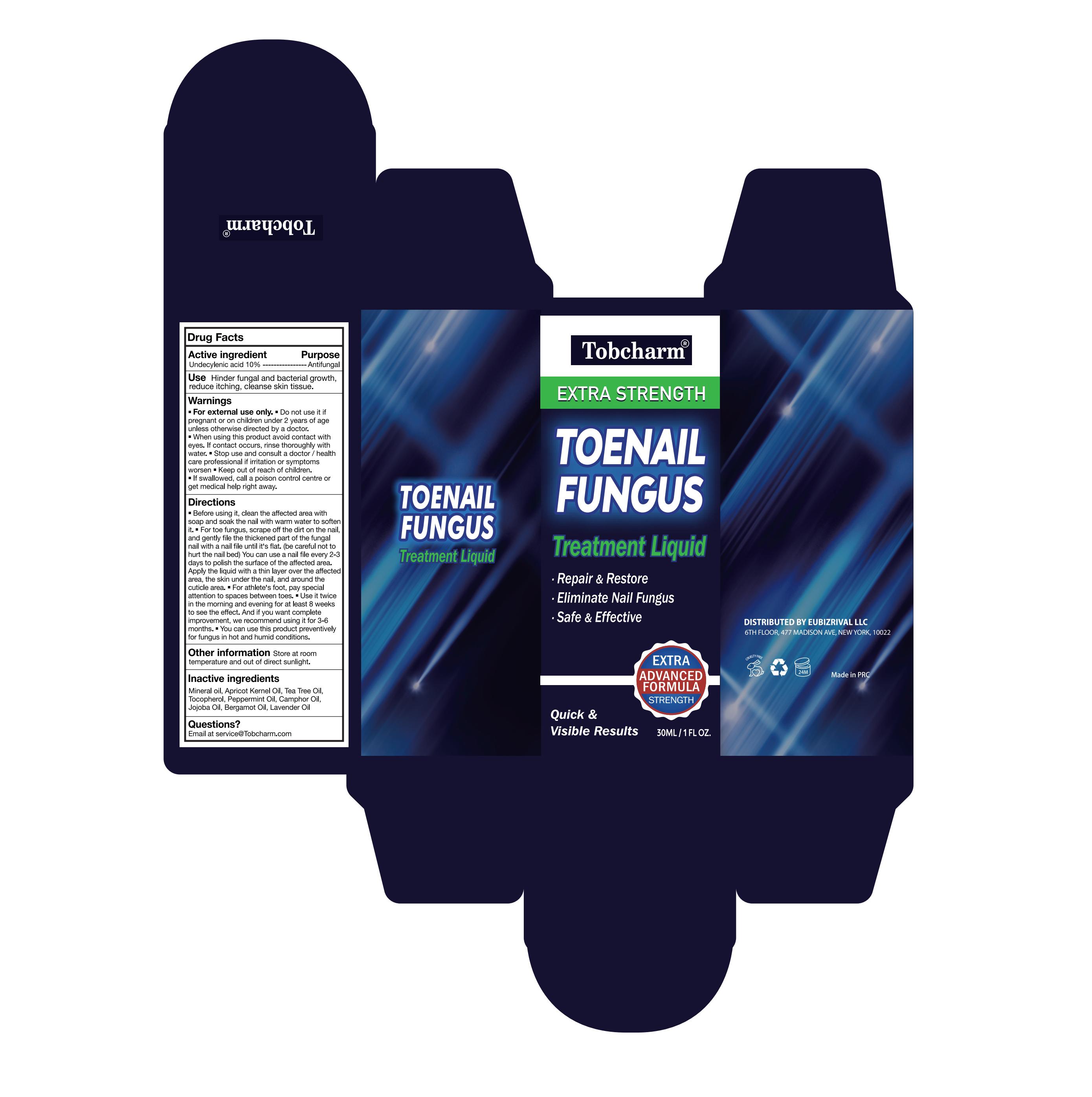 DRUG LABEL: Tobcharm Toenail Fungus Treatment Liquid
NDC: 85817-009 | Form: LIQUID
Manufacturer: Guangzhou Qiexiran Cosmetics Co., Ltd.
Category: otc | Type: HUMAN OTC DRUG LABEL
Date: 20251215

ACTIVE INGREDIENTS: MISOPROSTOL 10 g/100 mL
INACTIVE INGREDIENTS: PEPPERMINT OIL; TEA TREE OIL; APRICOT KERNEL OIL; TOCOPHEROL; BERGAMOT OIL; LAVENDER OIL; JOJOBA OIL; CAMPHOR OIL; MINERAL OIL

85817-009

Active Ingredient

Undecylenic acid 10%

Purpose

Antifungal

Use

Hinder fungal and bacterial growth, reduce itching, cleanse skin tissue.

Warnings

■ For external use only.

■ Do not use it if pregnant or on children under 2 years of age unless otherwise directed by a doctor.

When Using

■ When using this product avoid contact with eyes. If contact occurs, rinse thoroughly with water.

Stop Use

■ Stop use and consult a doctor / health care professional if irritation or symptoms worsen.

Ask Doctor

■ If swallowed, call a poison control centre or get medical help right away.

Keep Out Of Reach Of Children

Directions

■ Before using it, clean the affected area with soap and soak the nail with warm water to soften it.
■ For toe fungus, scrape off the dirt on the nail, and gently file the thickened part of the fungal nail with a nail file until it’s flat. (be careful not to hurt the nail bed) You can use a nail file every 2-3 days to polish the surface of the affected area.
Apply the liquid with a thin layer over the affected area, the skin under the nail, and around the cuticle area.
■ For athlete’s foot, pay special attention to spaces between toes.
■ Use it twice in the morning and evening for at least 8 weeks to see the effect. And if you want complete improvement, we recommend using it for 3-6 months.
■ You can use this product preventively for fungus in hot and humid conditions.

Other information

Store at room temperature and out of direct sunlight.

Inactive ingredients

Mineral oil, Apricot Kernel Oil, Tea Tree Oil, Tocopherol, Peppermint Oil, Camphor Oil, Jojoba Oil, Bergamot Oil, Lavender Oil

Questions

Email at service@Tobcharm.com